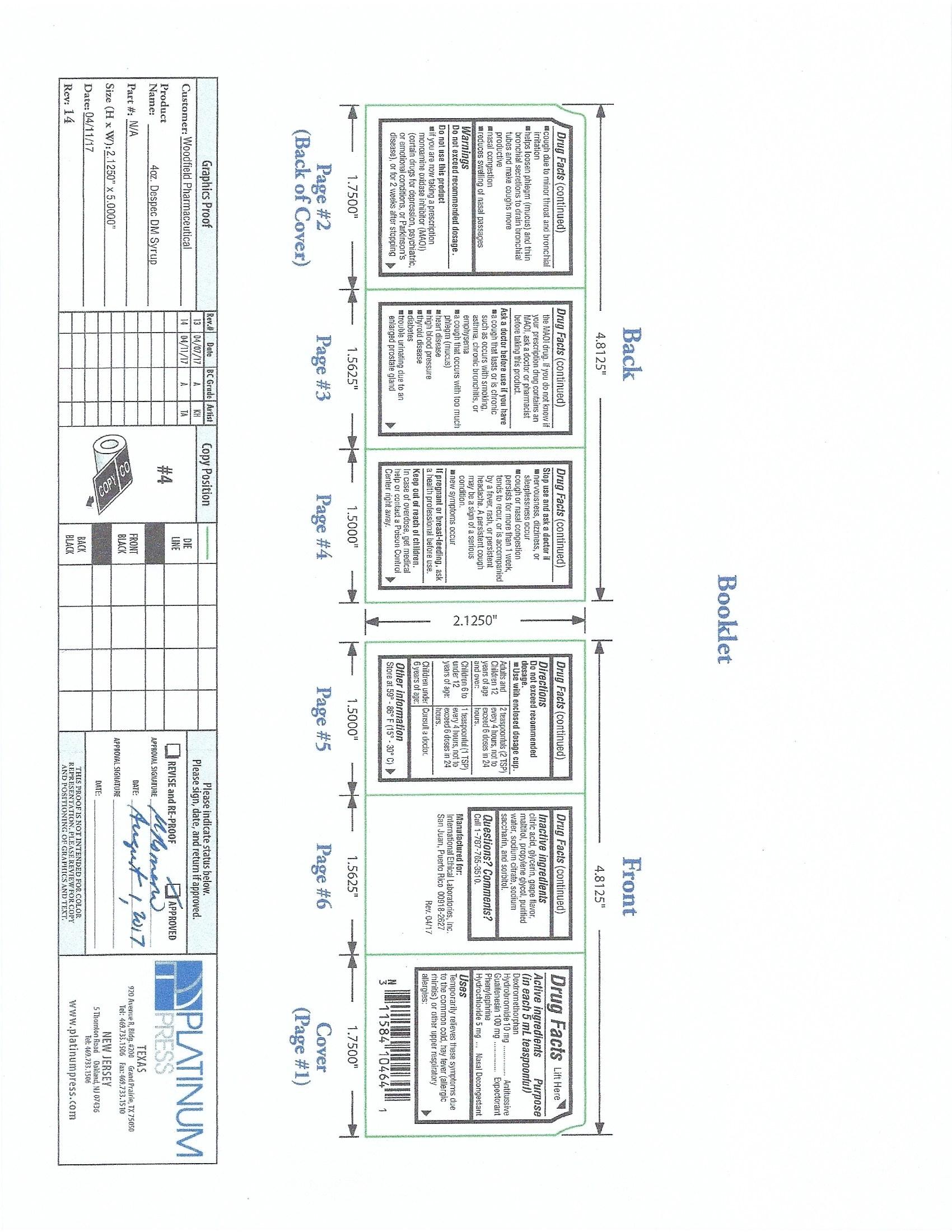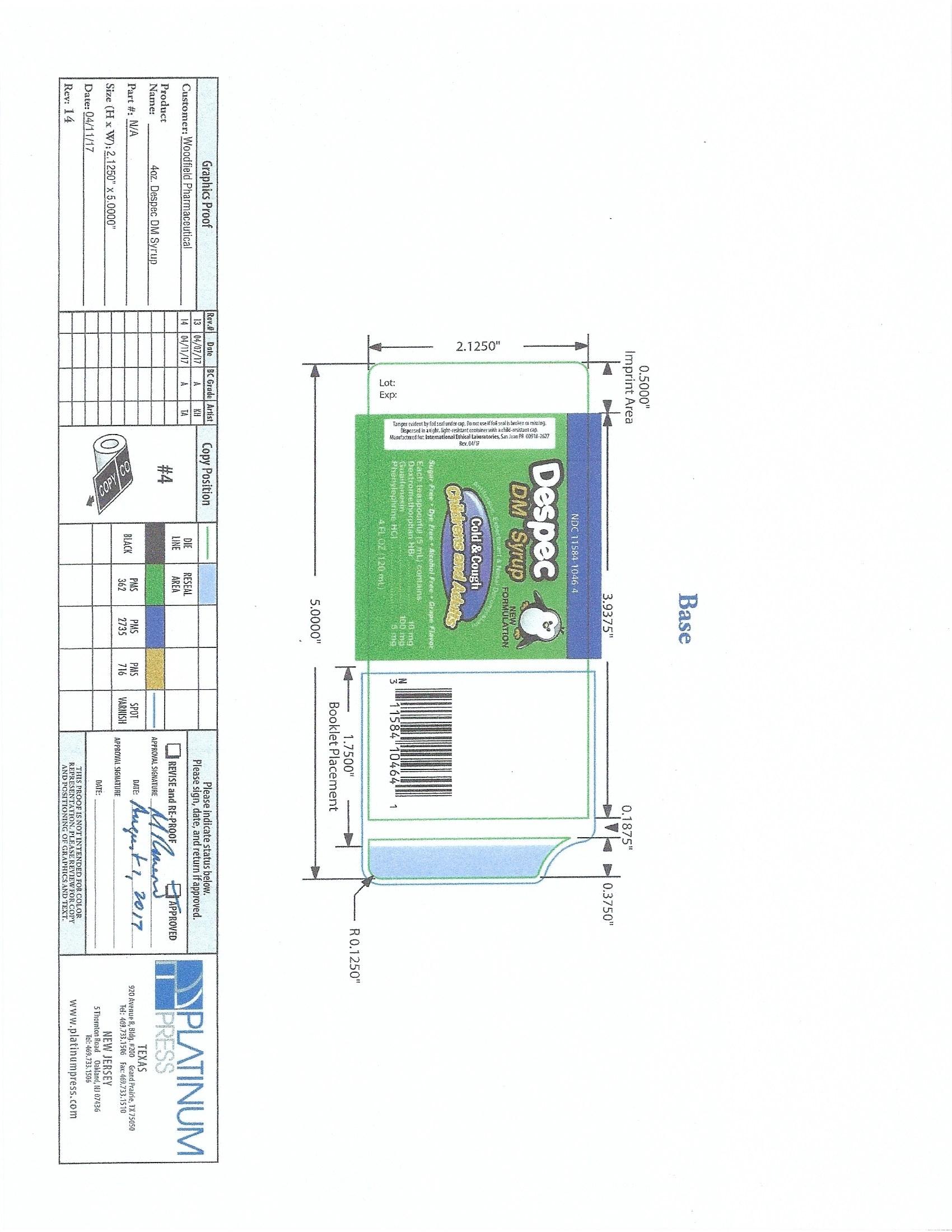 DRUG LABEL: DESPEC
NDC: 11584-1046 | Form: SYRUP
Manufacturer: International Ethical Laboratories, Inc
Category: otc | Type: HUMAN OTC DRUG LABEL
Date: 20211102

ACTIVE INGREDIENTS: DEXTROMETHORPHAN HYDROBROMIDE 10 mg/5 mL; GUAIFENESIN 100 mg/5 mL; PHENYLEPHRINE HYDROCHLORIDE 5 mg/5 mL
INACTIVE INGREDIENTS: CITRIC ACID MONOHYDRATE; PROPYLENE GLYCOL; WATER; MALTITOL; GLYCERIN; SODIUM CITRATE; SORBITOL

Despec DM

Drug Facts

Active ingredients (in each 5 mL teaspoonful)

Dextromethorphan Hydrobromide 10mg

Guaifenesin 100mg

Phenylephrine Hydrochloride 5mg

Purpose

Antitussive/ Expectroant/ Nasal Decongestant

Uses

Temporarily relieves these symptoms due to the common cold, hay fever (allergic rhinitis) or other upper respiratory allergies:

- cough due to minor throat and bronchial irritation
- helps loosen phlegm (mucus) and thin bronchial secretions to drain bronchial tubes and make coughs more productive
- nasal congestion
- reduces swelling of nasal passages

Warnings

Do not exceed recommended dosage

Do not use this product

- If you are now taking a prescription monoamine oxidase inhibitor (MAOI) (certain drugs for depression, psychiatric or emtional conditions, or Parkinson's disease). or for 2 weeks after stopping the MAOI drug. If you do not know if your prescription drug contains an MAOI, ask a doctor or pharmacist before taking this product.

Ask a doctor before use if you have

- a cough that lasts or is chronic such as occurs with smoking, asthma, chronic bronchitis, or emphysema
- a cough that occurs with too much phlegm (mucus)
- heart disease
- high blood pressure
- thyroid disease
- diabetes
- trouble urinating due to an enlarged prostate gland

Stop use and ask a doctor if

- nervousness, dizziness, or sleeplessness, occur
- cough or nasal congestion persists for more than 1 week, trends to recur, or persistent headache. A persistent cough may be a sign of a serious condition.
- new symptoms occur

If pregnant or breast-feeding

ask a health professional before use.

Keep out of reach of children

In case of overdose, get medical help or contact a Poison Control Center right away.

Directions

Do not exceed recommeneded dosage.

- Use with enclosed dosage cup.

Adults and children 12 years of age and over------2 teaspoonfuls (2 TSP) every 4 hours, not to exceed 6 doses in 24 hours.

Children 6 to under 12 years of age........1 teaspoonful (1 TSP) every 4 hours, not to exceed 6 doses in 24 hours.

Children under 6 years of age....... Consult a doctor

Other information

Store at room temperature 59°-86°F (15°-30°C)

Inactive ingredients

Citric acid, glycerin, grape flavor, maltitol, propylene glycol, purified water, sodium citrate, sodium saccharin and sorbitol.

Questions? Comments?

call 1-787-765-3510

Principal Display Panel-Label

Principal Display Panel-120 mL Bottle Label